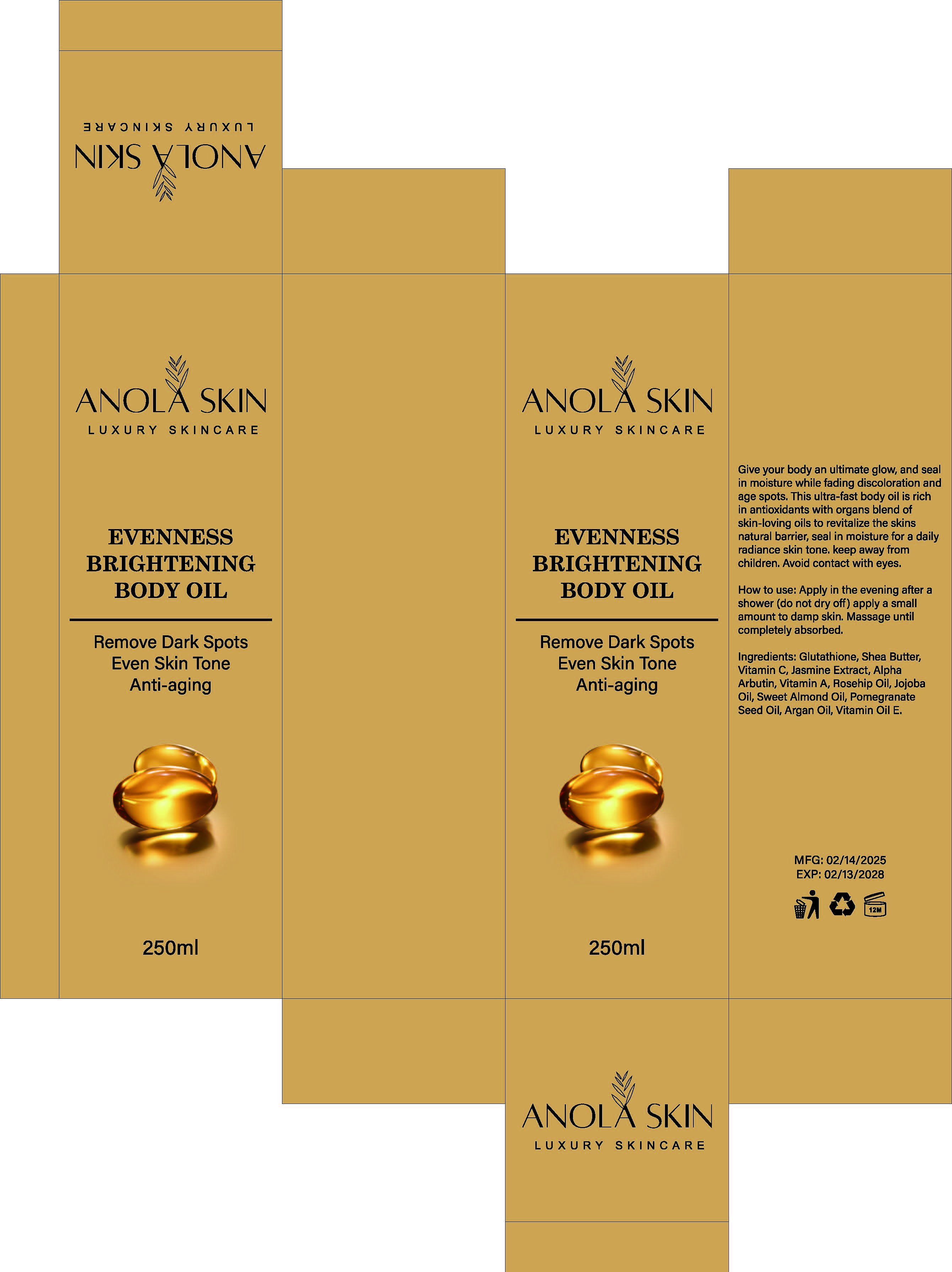 DRUG LABEL: EvennessBrighteningBodyOil
NDC: 84423-084 | Form: EMULSION
Manufacturer: Guangzhou Kadiya Biotechnology Co., Ltd.
Category: otc | Type: HUMAN OTC DRUG LABEL
Date: 20250731

ACTIVE INGREDIENTS: VITAMIN A 1.25 mg/250 mg; ASCORBIC ACID 7.5 mg/250 mg; GLUTATHIONE 5 mg/250 mg
INACTIVE INGREDIENTS: ROSA MOSCHATA OIL; JASMINUM OFFICINALE FLOWER; JOJOBA OIL; ARGAN OIL; ALPHA-TOCOPHEROL; ALMOND OIL; BUTYROSPERMUM PARKII (SHEA) OIL; ALPHA-ARBUTIN

PURPOSE

For skin whitening, antioxidant, moisturising

INACTIVE INGREDIENT

Shea Butter oil
Jasmine Extract
AlphaArbutin
Rosehip Oil
Jojoba Oil
Sweet Almond Oil
PomegranateSeed Oil
Argan Oil
Vitamin Oil E

Warning.
1.Before use, perform a skin test on your arm and discontinue use if you have allergy symptoms or skin abnormalities.
2、For external use only, avoid contact with eyes when used
3、Keep out of reach of children

INDICATIONS AND USAGE

Apply in the evening after a shower (do not dry off) apply a small amount to damp skin. Massage until completely absorbed.

DOSAGE AND ADMINISTRATION

apply a small amount to damp skin. Massage untilcompletely absorbed.

KEEP OUT OF REACH OF CHILDREN SECTION

Active Ingredients
Glutathione 2%
Vitamin C 3%
Vitamin A 0.5%

PACKAGE LABEL

Active Ingredients
Glutathione 2%
Vitamin C 3%
Vitamin A 0.5%

Uses：
For skin whitening, antioxidant, moisturising
The storage method：
Store sealed in a cool place and out of sunlight

Warning.
1.Before use, perform a skin test on your arm and discontinue use if you have allergy symptoms or skin abnormalities.
2、For external use only, avoid contact with eyes when used
3、Keep out of reach of children

Shea Butter oil, Jasmine Extract, AlphaArbutin, Rosehip Oil, Jojoba Oil, Sweet Almond Oil, PomegranateSeed Oil, Argan Oil, Vitamin Oil E